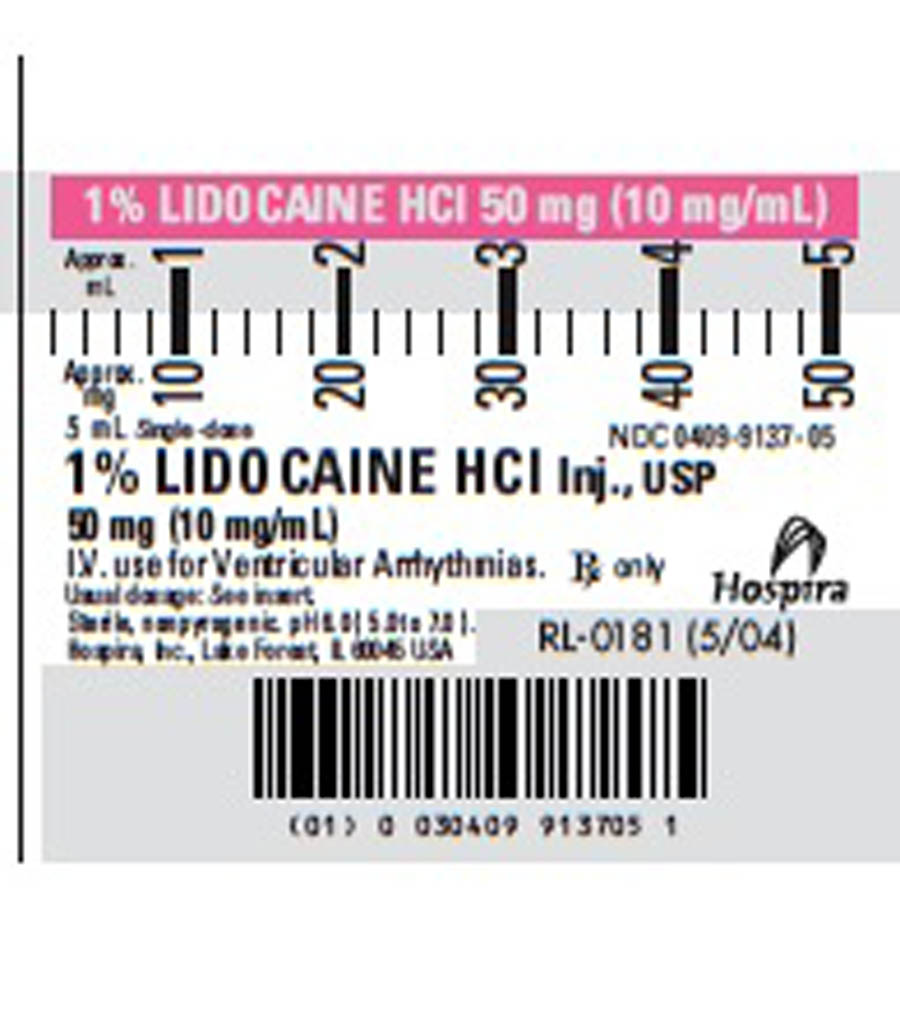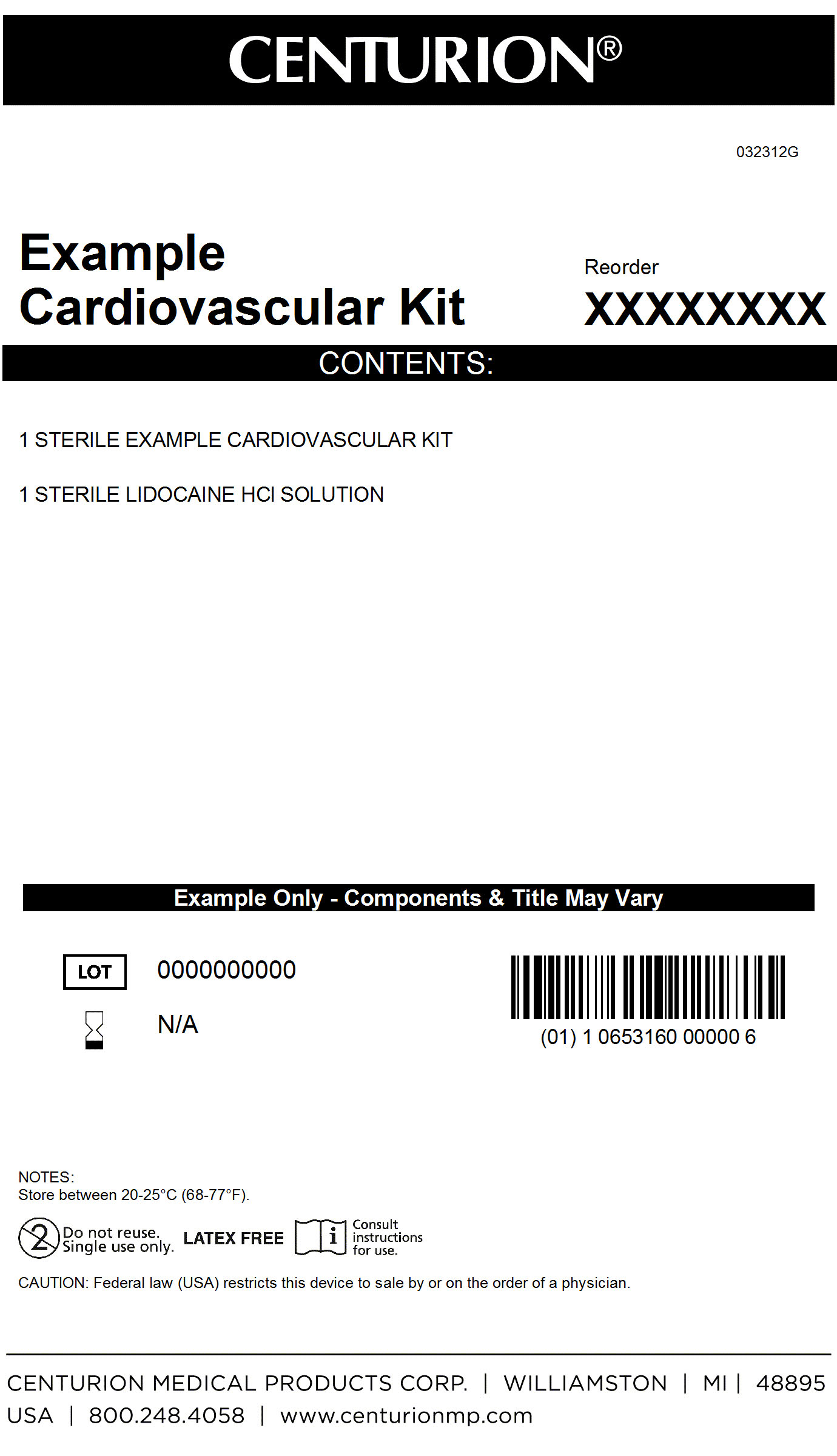 DRUG LABEL: Cardiovascular Procedure Kit
NDC: 24840-1105 | Form: KIT | Route: INTRAVENOUS
Manufacturer: Centurion Medical Products
Category: other | Type: MEDICAL DEVICE
Date: 20120529

ACTIVE INGREDIENTS: LIDOCAINE HYDROCHLORIDE 10 mg/1 mL
INACTIVE INGREDIENTS: SODIUM HYDROXIDE; HYDROCHLORIC ACID; SODIUM CHLORIDE

Cardiovascular Procedure Kit

Cardiovascular Kit Primary Label

MM1

Lidocaine Syringe Label

MM1